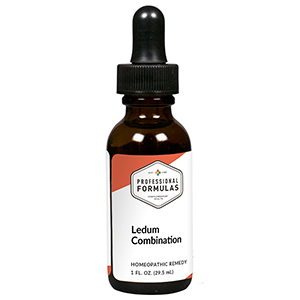 DRUG LABEL: Ledum Combination
NDC: 63083-9257 | Form: LIQUID
Manufacturer: Professional Complementary Health Formulas
Category: homeopathic | Type: HUMAN OTC DRUG LABEL
Date: 20190815

ACTIVE INGREDIENTS: PSEUDOGNAPHALIUM OBTUSIFOLIUM WHOLE 3 [hp_X]/29.5 mL; BERBERIS VULGARIS ROOT BARK 4 [hp_X]/29.5 mL; BLACK COHOSH 4 [hp_X]/29.5 mL; CINCHONA OFFICINALIS BARK 4 [hp_X]/29.5 mL; RHODODENDRON TOMENTOSUM LEAFY TWIG 4 [hp_X]/29.5 mL; RANUNCULUS BULBOSUS WHOLE 4 [hp_X]/29.5 mL; HORSE CHESTNUT 6 [hp_X]/29.5 mL; SODIUM BORATE 6 [hp_X]/29.5 mL; CITRULLUS COLOCYNTHIS FRUIT PULP 6 [hp_X]/29.5 mL; CUPRIC ACETATE 6 [hp_X]/29.5 mL; POTASSIUM CARBONATE 6 [hp_X]/29.5 mL; PICRIC ACID 6 [hp_X]/29.5 mL; PULSATILLA MONTANA WHOLE 6 [hp_X]/29.5 mL; CLAVICEPS PURPUREA SCLEROTIUM 6 [hp_X]/29.5 mL; SILICON DIOXIDE 6 [hp_X]/29.5 mL; AMMONIUM CATION 8 [hp_X]/29.5 mL; BOS TAURUS BONE MARROW 8 [hp_X]/29.5 mL; BOVINE TYPE II COLLAGEN (TRACHEAL CARTILAGE) 8 [hp_X]/29.5 mL; BOS TAURUS INTERVERTEBRAL DISC 8 [hp_X]/29.5 mL; SUS SCROFA ADRENAL GLAND 10 [hp_X]/29.5 mL; SILVER 10 [hp_X]/29.5 mL; ANHYDROUS DIBASIC CALCIUM PHOSPHATE 10 [hp_X]/29.5 mL; MERCURIC OXIDE 10 [hp_X]/29.5 mL; SEPIA OFFICINALIS JUICE 10 [hp_X]/29.5 mL; ZINC 10 [hp_X]/29.5 mL; GONORRHEAL URETHRAL SECRETION HUMAN 12 [hp_X]/29.5 mL; SULFUR 30 [hp_X]/29.5 mL
INACTIVE INGREDIENTS: ALCOHOL; WATER

R257

ACTIVE INGREDIENTS

Gnaphalium polycephalum 3X
Berberis vurgaris 4X
Cimicifuga racemosa 4X
Cinchona officinalis 4X
Ledum palustre 4X
Ranunculus bulbosus 4X
Aesculus hippocastanum 6X
Borax 6X
Colocynthis 6X
Cuprum aceticum 6X
Kali carbonicum 6X
Picricum acidum 6X
Pulsatilla 6X
Secale cornutum 6X
Silicea 6X
Ammonium muriaticum 8X
Bone marrow 8X
Cartilage 8X
Intervertebral disc 8X
Adrenal 10X
Argentum metallicum 10X
Calcarea phosphorica 10X
Mercurius praecipitatus ruber 10X
Sepia 10X
Zincum metallicum 10X
Medorrhinum 12X
Sulphur 30X

QUESTIONS

Professional Formulas

PO Box 2034 Lake Oswego, OR 97035

INDICATIONS

For the temporary relief of mild joint, muscle, or back pain, stiffness, or tenderness.*

PURPOSE

*Claims based on traditional homeopathic practice, not accepted medical evidence. Not FDA evaluated.

WARNINGS

In case of overdose, get medical help or contact a poison control center right away.

Keep out of the reach of children.

PREGNANCY OR BREAST FEEDING

If pregnant or breastfeeding, ask a healthcare professional before use.

DIRECTIONS

Place drops under tongue 30 minutes before/after meals. Adults and children 12 years and over: Take 10 drops up to 3 times per day. Consult a physician for use in children under 12 years of age.

OTHER INFORMATION

Tamper resistant. If seal is broken, do not use. After opening, close container tightly and store at room temperature away from heat.

INACTIVE INGREDIENTS

40% ethanol, purified water.

LABEL

Est 1985

Professional Formulas

Complementary Health

Ledum Combination

Homeopathic Remedy

1 FL. OZ. (29.5 mL)